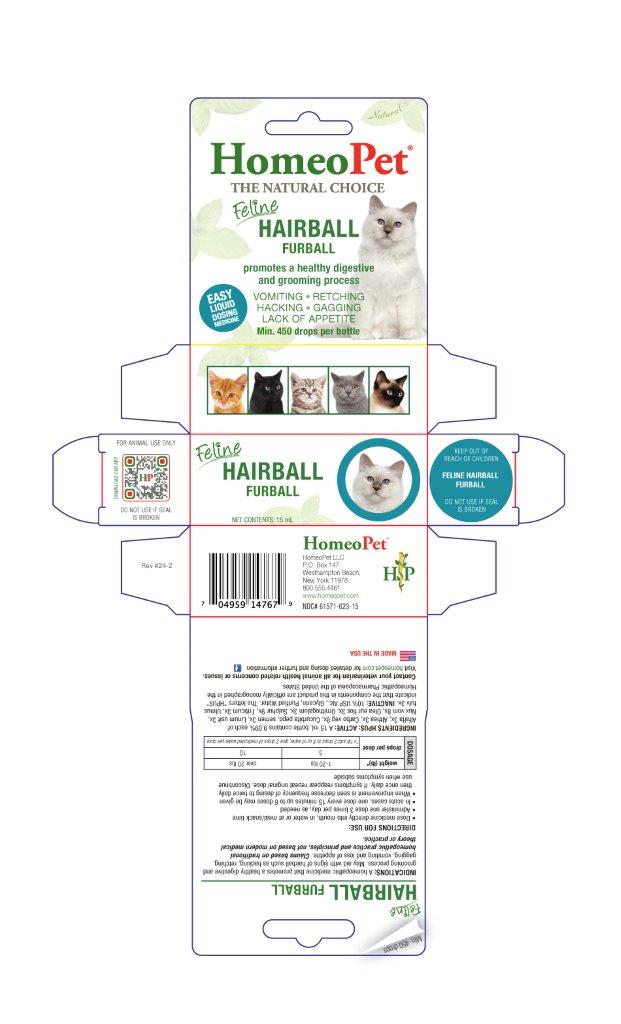 DRUG LABEL: Hairball
NDC: 61571-623 | Form: LIQUID
Manufacturer: HomeoPet, LLC
Category: homeopathic | Type: OTC ANIMAL DRUG LABEL
Date: 20241121

ACTIVE INGREDIENTS: ALFALFA 3 [hp_X]/15 mL; ALTHAEA OFFICINALIS ROOT 3 [hp_X]/15 mL; ACTIVATED CHARCOAL 8 [hp_X]/15 mL; PUMPKIN SEED 3 [hp_X]/15 mL; FLAX SEED 3 [hp_X]/15 mL; STRYCHNOS NUX-VOMICA SEED 8 [hp_X]/15 mL; OLEA EUROPAEA FLOWER 3 [hp_X]/15 mL; ORNITHOGALUM UMBELLATUM 3 [hp_X]/15 mL; SULFUR 9 [hp_X]/15 mL; ELYMUS REPENS ROOT 3 [hp_X]/15 mL; ULMUS RUBRA BARK 3 [hp_X]/15 mL
INACTIVE INGREDIENTS: ALCOHOL; GLYCERIN; WATER

Feline Hairball

Feline Hairball

Promotes a healthy digestive and grooming process

VOMITING-RETCHING-HACKING-GAGGING-LACK OF APPETITE

INDICATIONS

A homeopathic medicine that promotes a healthy digestive and grooming process. May aid iwth signs of hairball such as hacking, retching, gagging, vomiting and loss of appetite. Claims based on traditional homeopathic practice and principles, not based on modern medical theory or practice.

Directions for Use and Dosing

- Dose remedy directly into mouth, in water or at meal/snack time

- Administer one dose 3 times per day, as needed

- In acute cases, one dose every 15 minutes up to 6 doses may be given

- When improvement is seen decrease frequency of dosing to twice daily, then once daily. If symptoms reappear repeat original dose. Discontinue use when symptoms subside

Dosage | weight (lb)* | 1-20 lbs | over 20 lbs
Dosage | drops per dose | 5 | 10
Dosage | drops per dose | *<1 lb add 2 drops to 8 oz of water, give 2 drops of medicated water per dose

INGREDIENTS HPUS: ACTIVE

Alfalfa 3x, Althea 3x, Carbo veg 8x, Cucurbita pepo, semen 3x, Linum usit 3x, Nux vom 8x, Olea eur, flos 3x, Ornithogalum 3x, Sulphur 9x, Triticum 3x, Ulmus fulv 3x.

INACTIVE

USP Alcohol, Glycerin, Purified water

ASK DOCTOR

Contact your veterinarian for all animal health related concerns or issues.

Visit homeopet.com for detailed dosing and further information.

PACKAGE LABEL

Add image transcription here...